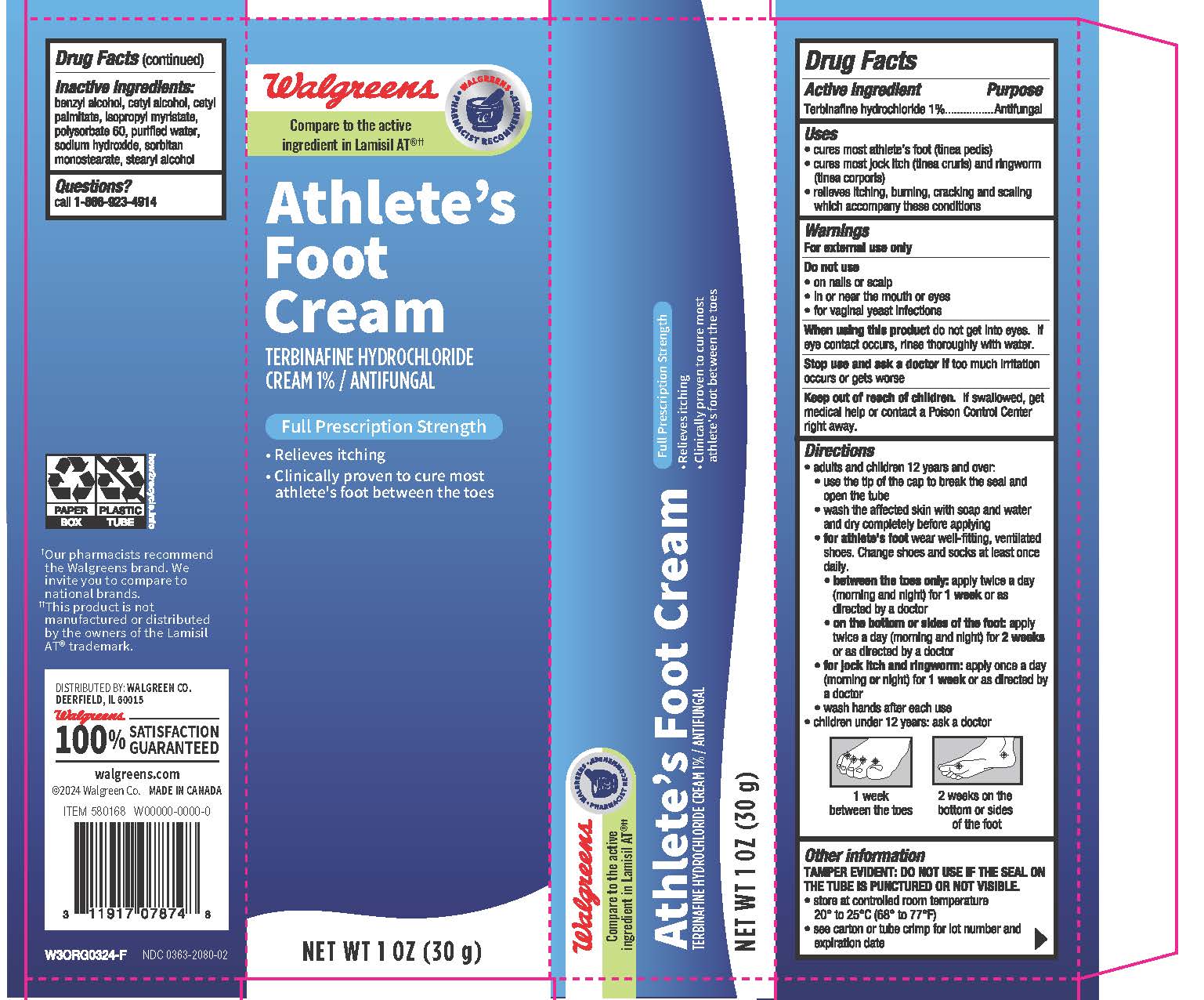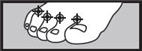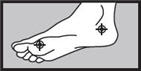 DRUG LABEL: Walgreens
NDC: 0363-2080 | Form: CREAM
Manufacturer: Walgreen Company
Category: otc | Type: HUMAN OTC DRUG LABEL
Date: 20251126

ACTIVE INGREDIENTS: TERBINAFINE HYDROCHLORIDE 1 g/100 g
INACTIVE INGREDIENTS: BENZYL ALCOHOL; CETYL ALCOHOL; CETYL PALMITATE; ISOPROPYL MYRISTATE; POLYSORBATE 60; WATER; SODIUM HYDROXIDE; SORBITAN MONOSTEARATE; STEARYL ALCOHOL

Walgreens
Athlete's Foot

Drug Facts

Active ingredient

Terbinafine hydrochloride 1%

Purpose

Antifungal

Uses

- cures most athlete's foot (tinea pedis)
- cures most jock itch (tinea cruris) and ringworm (tinea corporis)
- relieves itching, burning, cracking and scaling which accompany these conditions

Warnings

For external use only

Do not use

- on nails or scalp
- in or near the mouth or the eyes
- for vaginal yeast infections

WHEN USING

When using this productdo not get into the eyes. If eye contact occurs, rinse thoroughly with water.

Stop use and ask a doctor if

- too much irritation occurs or gets worse.

Keep out of reach of children.If swallowed, get medical help or contact a poison control center right away.

Directions

- adults and children 12 years and older
  - use the tip of the cap to break the seal and open the tube
  - wash the affected skin with soap and water and dry completely before applying
  - for athlete's footwear well-fitting, ventilated shoes. Change shoes and socks at least once daily.
    - between the toes only:apply twice a day (morning and night) for 1 weekor as directed by a doctor.
    - on the bottom or sides of the foot:apply twice a day (morning and night) for 2 weeksor as directed by a doctor.
  - for jock itch and ringworm:apply once a day (morning ornight) for 1 weekor as directed by a doctor.
  - wash hands after each use
- children under 12 years: ask a doctor

1 week between the toes
2 weeks on the bottom or sides of the foot

Other information

- do not use if seal on tube is broken or is not visible
- store at controlled room temperature 20°-25°C (68°-77°F)
- see carton or tube crimp for lot number and expiration date

Inactive ingredients

benzyl alcohol, cetyl alcohol, cetyl palmitate, isopropyl myristate, polysorbate 60, purified water, sodium hydroxide, sorbitan monostearate, stearyl alcohol.

Questions?

Call 1-866-923-4914

DISTRIBUTED BY:
WALGREEN CO.
200 WILMOT RD.,
DEERFIELD, IL 60015

PRINCIPAL DISPLAY PANEL - 15 g Tube Carton

Walgreens

Athlete's Foot Cream

TERBINAFINE HYDROCHLORIDE 1% / ANTIFUNGAL CREAM

NET WT 0.5 OZ (15 g)